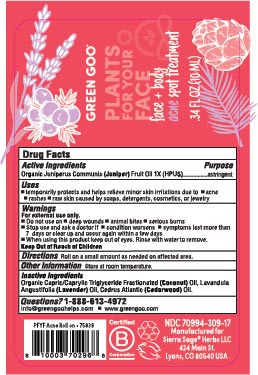 DRUG LABEL: Acne Roll On
NDC: 70994-310 | Form: OIL
Manufacturer: Spry Life LLC
Category: homeopathic | Type: HUMAN OTC DRUG LABEL
Date: 20251215

ACTIVE INGREDIENTS: JUNIPER BERRY OIL 1 [hp_X]/100 mL
INACTIVE INGREDIENTS: COCONUT OIL; LAVENDER OIL; CEDRUS ATLANTICA BARK OIL

Acne Roll On

Purpose

Astringent

Active Ingredients

Organic Juniperus Communis (Juniper) Fruit Oil

Indications & Dosage

■ temporarily protects and helps relieve minor skin irritation and itching due to

■ acne ■ rashes ■ raw skin caused by soaps, detergents, cosmetics, or jewelry

Warnings

For external use only.

■ Do not use on ■ deep wounds ■ animal bites ■ serious burns

■ Stop use and ask a doctor if ■ condition worsens ■ symptoms last more than

7 days or clear up and occur again within a few days

■ When using this product keep out of eyes. Rinse with water to remove.

Keep out of Reach of Children

Dosage & Administration

Roll on a small amount as needed on affected area.

Storage

Store at Room Temperature.

Inactive Ingredients

Organic Capric/Caprylic Triglyceride Fractionated (Coconut) Oil, Lavandula

Angustifolia (Lavender) Oil, Cedrus Atlantic (Cedarwood) Oil.

Questions

1-888-613-4972

info@greengoohelps.com ■ www.greengoo.com